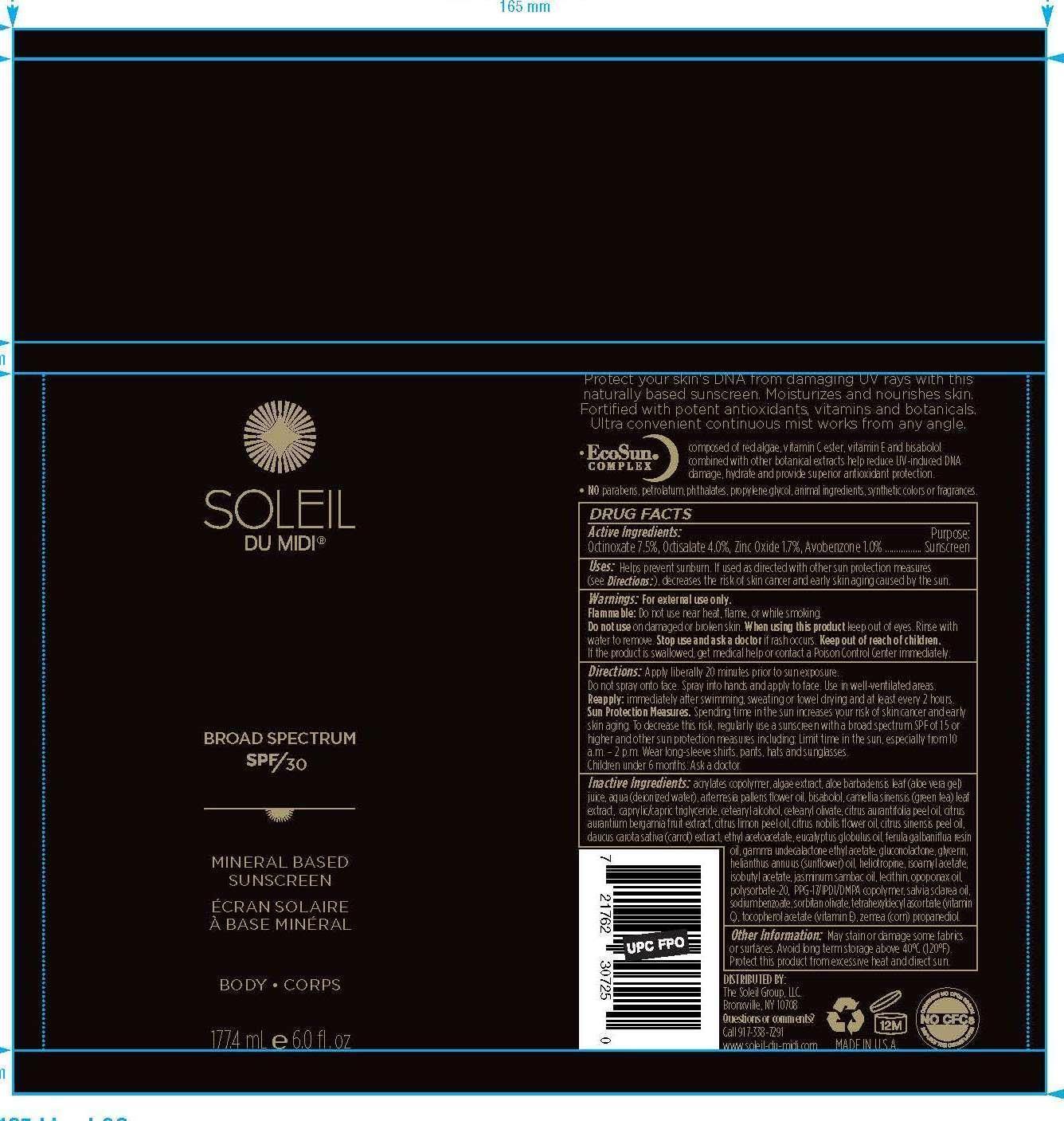 DRUG LABEL: Soleil Broad Spectrum SPF-30
NDC: 69630-002 | Form: SPRAY
Manufacturer: The Soleil Group, LLC
Category: otc | Type: HUMAN OTC DRUG LABEL
Date: 20150226

ACTIVE INGREDIENTS: OCTINOXATE 7.4 mg/1 mL; OCTISALATE 4 mg/1 mL; ZINC OXIDE 1.7 mg/1 mL; AVOBENZONE 1 mg/1 mL
INACTIVE INGREDIENTS: METHACRYLATE/METHOXY PEG-10 MALEATE/STYRENE COPOLYMER; FUCUS VESICULOSUS; ALOE VERA LEAF; water; ARTEMISIA PALLENS WHOLE; LEVOMENOL; GREEN TEA LEAF; CAPRYLIC/CAPRIC/LINOLEIC TRIGLYCERIDE; CETYL ALCOHOL; CETEARYL OLIVATE; CITRUS AURANTIUM FLOWER OIL; CITRUS AURANTIUM FRUIT; CITRUS LIMON FRUIT OIL; CITRUS NOBILIS; CITRUS SINENSIS FRUIT OIL; CARROT; ETHYL ACETOACETATE; EUCALYPTUS GLOBULUS WHOLE; GLUCONOLACTONE; GLYCERIN; SUNFLOWER OIL; PIPERONAL; ISOAMYL ACETATE; ISOBUTYL ACETATE; JASMINUM SAMBAC WHOLE; LECITHIN, SOYBEAN; OPOPANAX CHIRONIUM WHOLE; POLYSORBATE 20; PEG/PPG-17/6 COPOLYMER; SALVIA SCLAREA SEED OIL; SODIUM BENZOATE; SORBITAN OLIVATE; TETRAHEXYLDECYL ASCORBATE; .ALPHA.-TOCOPHEROL ACETATE; PROPANEDIOL

Soleil SPF-30

WARNINGS

For external use only. Flammable: Do not use
near heat, flame, or while smoking. Do not use on damaged
or broken skin. When using this product keep out of eyes.
Rinse with water to remove. Stop use and ask a doctor if rash
occurs. Keep out of reach of children. If the product is
swallowed, get medical help or contact a Poison Control
Center immediately.

Keep out of reach of children

ACTIVE INGREDIENT

Octinoxate 5.0%, Octisalate
3.0%, Zinc Oxide 2.5%

Uses

Helps prevent sunburn. If used as directed with other
sun protection measures (see Directions:), decreases the risk
of skin cancer and early skin aging caused by the sun.

PURPOSE

Sunscreen

Directions

Apply liberally 20 minutes prior to sun
exposure. Do not spray onto face. Spray into hands and apply
to face. Use in well-ventilated areas. Reapply: immediately
after swimming, sweating or towel drying and at least every 2
hours. Sun Protection Measures. Spending time in the sun
increases your risk of skin cancer and early skin aging. To
decrease this risk, regularly use a sunscreen with a broad
spectrum SPF of 15 or higher and other sun protection
measures including: Limit time in the sun, especially from 10
a.m. – 2 p.m. Wear long-sleeve shirts, pants, hats and
sunglasses. Children under 6 months: Ask a doctor.

Other Information

May stain or damage some fabrics or
surfaces. Avoid long term storage above 40°C (120°F).
Protect this product from excessive heat and direct sun.